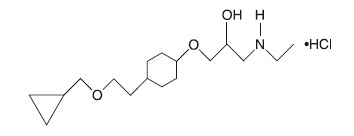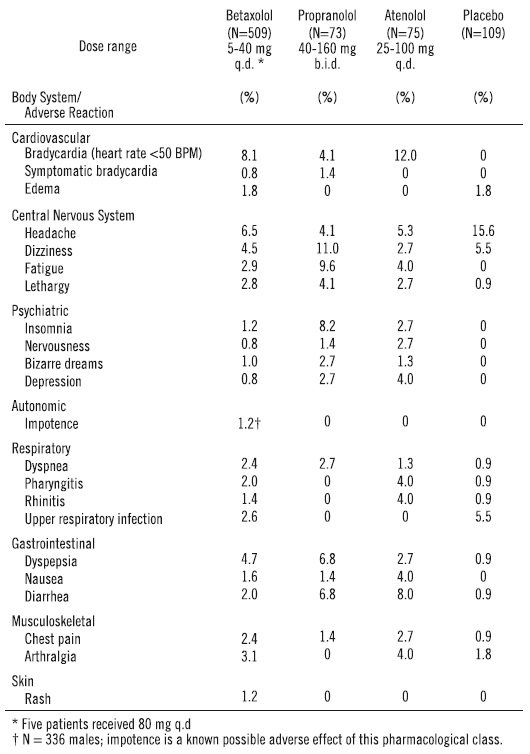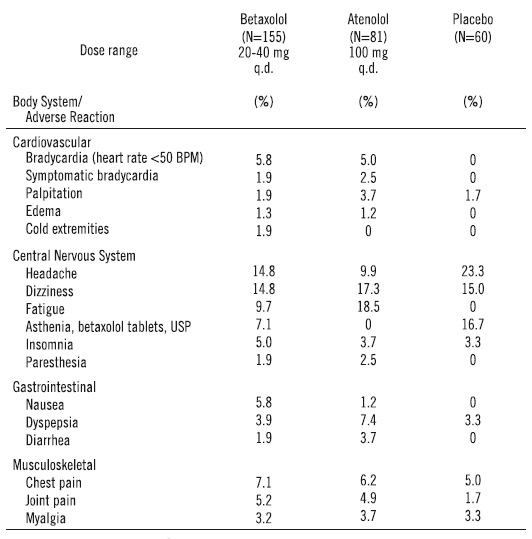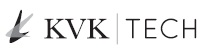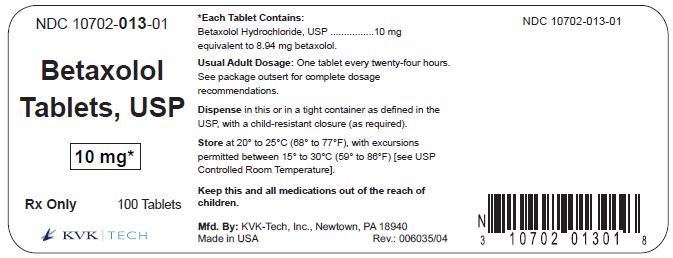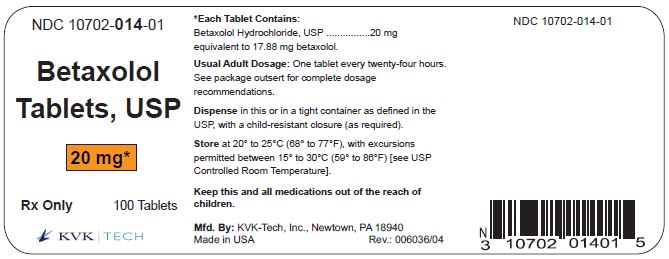 DRUG LABEL: BETAXOLOL HYDROCHLORIDE
NDC: 10702-013 | Form: TABLET, COATED
Manufacturer: KVK-TECH, INC.
Category: prescription | Type: HUMAN PRESCRIPTION DRUG LABEL
Date: 20240430

ACTIVE INGREDIENTS: BETAXOLOL HYDROCHLORIDE 10 mg/1 1
INACTIVE INGREDIENTS: ANHYDROUS LACTOSE; CELLULOSE, MICROCRYSTALLINE; STARCH, CORN; SODIUM STARCH GLYCOLATE TYPE A POTATO; STEARIC ACID; TITANIUM DIOXIDE; POLYETHYLENE GLYCOL 400; POLYSORBATE 80; HYPROMELLOSE 2910 (6 MPA.S)

Betaxolol Tablets, USP

DESCRIPTION:

Betaxolol hydrochloride is a ß1-selective (cardioselective) adrenergic receptor blocking agent available as 10-mg and 20-mg tablets for oral administration. Betaxolol hydrochloride is chemically described as 2-propanol, 1- [4-[2-(cyclopropylmethoxy) ethyl] phenoxy]-3-[(1-methylethyl) amino]-, hydrochloride, (±)-. It has the following chemical structure:

Each tablet for oral administration contains 10 mg or 20 mg of betaxolol hydrochloride equivalent to 8.94 mg or 17.88 mg of betaxolol respectively. In addition, each tablet contains the following inactive ingredients, hypromellose, anhydrous lactose, microcrystalline cellulose, polyethylene glycol, polysorbate 80, pregelatinized starch, sodium starch glycolate, stearic acid and titanium dioxide.

Betaxolol hydrochloride is a water-soluble white crystalline powder with a molecular formula of C18H29NO3•HCl and a molecular weight of 343.9. It is freely soluble in water, ethanol, chloroform, and methanol, and has a pKa of 9.4.

CLINICAL PHARMACOLOGY:

Betaxolol is a ß1-selective (cardioselective) adrenergic receptor blocking agent that has weak membrane-stabilizing activity and no intrinsic sympathomimetic (partial agonist) activity. The preferential effect on ß1 receptors is not absolute, however, and some inhibitory effects on ß2 receptors (found chiefly in the bronchial and vascular musculature) can be expected at higher doses.

Pharmacokinetics and Metabolism: In man, absorption of an oral dose is complete. There is a small and consistent first-pass effect resulting in an absolute bioavailability of 89% ± 5% that is unaffected by the concomitant ingestion of food or alcohol. Mean peak blood concentrations of 21.6 ng/ml (range 16.3 to 27.9 ng/ml) are reached between 1.5 and 6 (mean about 3) hours after a single oral dose, in healthy volunteers, of 10 mg of betaxolol. Peak concentrations for 20-mg and 40-mg doses are 2 and 4 times that of a 10-mg dose and have been shown to be linear over the dose range of 5 to 40 mg. The peak to trough ratio of plasma concentrations over 24 hours is 2.7. The mean elimination half-life in various studies in normal volunteers ranged from about 14 to 22 hours after single oral doses and is similar in chronic dosing. Steady state plasma concentrations are attained after 5 to 7 days with once-daily dosing in persons with normal renal function.

Betaxolol is approximately 50% bound to plasma proteins. It is eliminated primarily by liver metabolism and secondarily by renal excretion. Following oral administration, greater than 80% of a dose is recovered in the urine as betaxolol and its metabolites. Approximately 15% of the dose administered is excreted as unchanged drug, the remainder being metabolites whose contribution to the clinical effect is negligible.

Steady state studies in normal volunteers and hypertensive patients found no important differences in kinetics. In patients with hepatic disease, elimination half-life was prolonged by about 33%, but clearance was unchanged, leading to little change in AUC. Dosage reductions have not routinely been necessary in these patients. In patients with chronic renal failure undergoing dialysis, mean elimination half-life was approximately doubled, as was AUC, indicating the need for a lower initial dosage (5 mg) in these patients. The clearance of betaxolol by hemodialysis was 0.015 L/h/kg and by peritoneal dialysis, 0.010 L/h/kg. In one study (n=8), patients with stable renal failure, not on dialysis, with mean creatinine clearance of 27 ml/min showed slight increases in elimination half-life and AUC, but no change in Cmax. In a second study of 30 hypertensive patients with mild to severe renal impairment, there was a reduction in clearance of betaxolol with increasing degrees of renal insufficiency. Inulin clearance (mL/min/1.73 m^2) ranged from 70 to 107 in 7 patients with mild impairment, 41 to 69 in 14 patients with moderate impairment, and 8 to 37 in 9 patients with severe impairment. Clearance following oral dosing was reduced significantly in patients with moderate and severe renal impairment (26% and 35%, respectively) when compared with those with mildly impaired renal function. In the severely impaired group, the mean Cmax and the mean elimination half-life tended to increase (28% and 24%, respectively) when compared with the mildly impaired group. A starting dose of 5 mg is recommended in patients with severe renal impairment. (See Dosage and Administration.)

Studies in elderly patients (n=10) gave inconsistent results but suggest some impairment of elimination, with one small study (n=4) finding a mean half-life of 30 hours. A starting dose of 5 mg is suggested in older patients.

Pharmacodynamics: Clinical pharmacology studies have demonstrated the beta-adrenergic receptor blocking activity of betaxolol by (1) reduction in resting and exercise heart rate, cardiac output, and cardiac work load, (2) reduction of systolic and diastolic blood pressure at rest and during exercise, (3) inhibition of isoproterenol-induced tachycardia, and (4) reduction of reflex orthostatic tachycardia.

The ß1-selectivity of betaxolol in man was shown in three ways: (1) In normal subjects, 10 and 40 mg oral doses of betaxolol tablets, USP, which reduced resting heart rate at least as much as 40 mg of propranolol, produced less inhibition of isoproterenol-induced increases in forearm blood flow and finger tremor than propranolol. In this study, 10 mg of betaxolol tablets, USP was at least comparable to 50 mg of atenolol. Both doses of betaxolol tablets, USP, and the one dose of atenolol, however, had more effect on the isoproterenol-induced changes than placebo (indicating some ß2 effect at clinical doses) and the higher dose of betaxolol tablets, USP was more inhibitory than the lower. (2) In normal subjects, single intravenous doses of betaxolol and propranolol, which produced equal effects on exercise-induced tachycardia, had differing effects on insulin-induced hypoglycemia, with propranolol, but not betaxolol, prolonging the hypoglycemia compared with placebo. Neither drug affected the maximum extent of the hypoglycemic response. (3) In a single-blind crossover study in asthmatics (n=10), intravenous infusion over 30 minutes of low doses of betaxolol (1.5 mg) and propranolol (2 mg) had similar effects on resting heart rate but had differing effects on FEV1 and forced vital capacity, with propranolol causing statistically significant (10% to 20%) reductions from baseline in mean values for both parameters while betaxolol had no effect on mean values. While blood levels were not measured, the dose of betaxolol used in this study would be expected to produce blood concentrations, at the time of the pulmonary function studies, considerably lower than those achieved during antihypertensive therapy with recommended doses of betaxolol. In a randomized double-blind, placebo-controlled crossover (4X4 Latin Square) study in 10 asthmatics, betaxolol (about 5 or 10 mg IV) had little effect on isoproterenol-induced increases in FEV1; in contrast, propranolol (about 7 mg IV) inhibited the response.

Consistent with the negative chronotropic effect, due to beta-blockade of the SA node, and lack of intrinsic sympathomimetic activity, betaxolol increases sinus cycle length and sinus node recovery time. Conduction in the AV node is also prolonged.

Significant reductions in blood pressure and heart rate were observed 24 hours after dosing in double-blind, placebo-controlled trials with doses of 5 to 40 mg administered once daily. The antihypertensive response to betaxolol tablets, USP was similar at peak blood levels (3 to 4 hours) and at trough (24 hours). In a large randomized, parallel dose-response study of 5, 10, and 20 mg, the antihypertensive effects of the 5 mg dose were roughly half of the effects of the 20 mg dose (after adjustment for placebo effects) and the 10 mg dose gave more than 80% of the antihypertensive response to the 20 mg dose. The effect of increasing the dose from 10 mg to 20 mg was thus small. In this study, while the antihypertensive response to betaxolol tablets, USP showed a dose-response relationship, the heart rate response (reduction in HR) was not dose related. In other trials, there was little evidence of a greater antihypertensive response to 40 mg than to 20 mg. The maximum effect of each dose was achieved within 1 or 2 weeks. In comparative trials against propranolol, atenolol, and chlorthalidone, betaxolol tablets, USP appeared to be at least as effective as the comparative agent.

Betaxolol tablets, USP has been studied in combination with thiazide-type diuretics and the blood pressure effects of the combination appear additive. Betaxolol tablets, USP has also been used concurrently with methyldopa, hydralazine, and prazosin.

The mechanism of the antihypertensive effects of beta-adrenergic receptor blocking agents has not been established. Several possible mechanisms have been proposed, however, including: (1) competitive antagonism established. Several possible mechanisms have been proposed, however, including: (1) competitive antagonism of catecholamines at peripheral (especially cardiac) adrenergic-neuronal sites, leading to decreased cardiac output, (2) a central effect leading to reduced sympathetic outflow to the periphery, and (3) suppression of rennin activity.

The results from long-term studies have not shown any diminution of the antihypertensive effect of betaxolol tablets, USP with prolonged use.

INDICATIONS AND USAGE:

Betaxolol tablets, USP is indicated in the management of hypertension. It may be used alone or concomitantly with other antihypertensive agents, particularly thiazide-type diuretics.

CONTRAINDICATIONS:

Betaxolol tablets, USP is contraindicated in patients with known hypersensitivity to the drug.

Betaxolol tablets, USP is contraindicated in patients with sinus bradycardia, heart block greater than first degree, cardiogenic shock, and overt cardiac failure (see Warnings).

WARNINGS:

Cardiac Failure: Sympathetic stimulation may be a vital component supporting circulatory function in congestive heart failure, and beta-adrenergic receptor blockade carries the potential hazard of further depressing myocardial contractility and precipitating more severe heart failure. In hypertensive patients who have congestive heart failure controlled by digitalis and diuretics, beta-blockers should be administered cautiously. Both digitalis and beta-adrenergic receptor blocking agents slow AV conduction.

In Patients Without a History of Cardiac Failure: Continued depression of the myocardium with beta-blocking agents over a period of time can, in some cases, lead to cardiac failure. Therefore, at the first sign or symptom of cardiac failure, discontinuation of betaxolol tablets, USP should be considered. In some cases beta-blocker therapy can be continued while cardiac failure is treated with cardiac glycosides, diuretics, and other agents, as appropriate.

Exacerbation of Angina Pectoris Upon Withdrawal: Abrupt cessation of therapy with certain beta-blocking agents in patients with coronary artery disease has been followed by exacerbations of angina pectoris and, in some cases, myocardial infarction has been reported. Therefore such patients should be warned against interruption of therapy without the physician’s advice. Even in the absence of overt angina pectoris, when discontinuation of betaxolol tablets, USP is planned, the patient should be carefully observed and therapy should be reinstituted, at least temporarily, if withdrawal symptoms occur.

Bronchospastic diseases: PATIENTS WITH BRONCHOSPASTIC DISEASE SHOULD NOT IN GENERAL RECEIVE BETA-BLOCKERS. Because of its relative ß1 selectivity (cardioselectivity), low doses of betaxolol tablets, USP may be used with caution in patients with bronchospastic disease who do not respond to or cannot tolerate alternative treatment. Since ß1 selectivity is not absolute and is inversely related to dose, the lowest possible dose of betaxolol tablets, USP should be used (5 to 10 mg once daily) and a bronchodilator should be made available. If dosage must be increased, divided dosage should be considered to avoid the higher peak blood levels associated with once-daily dosing.

Major Surgery: Chronically administered beta-blocking therapy should not be routinely withdrawn prior to major surgery, however the impaired ability of the heart to respond to reflex adrenergic stimuli may augment the risks of general anesthesia and surgical procedures (see Precautions, Drug Interactions). Titrate betaxolol dose to maintain effective heart rate control while avoiding frank hypotension and bradycardia.

Diabetes and Hypoglycemia: Beta-blockers should be used with caution in diabetic patients. Beta-blockers may mask tachycardia occurring with hypoglycemia (patients should be warned of this), although other manifestations such as dizziness and sweating may not be significantly affected. Unlike nonselective beta-blockers, betaxolol such as dizziness and sweating may not be significantly affected. Unlike nonselective beta-blockers, betaxolol tablets, USP does not prolong insulin-induced hypoglycemia.

Thyrotoxicosis: Beta-adrenergic blockade may mask certain clinical signs of hyperthyroidism (e.g., tachycardia). Abrupt withdrawal of beta-blockade might precipitate a thyroid storm; therefore, patients known or suspected of being thyrotoxic from whom betaxolol tablets, USP is to be withdrawn should be monitored closely (see DOSAGE AND ADMINISTRATION: Cessation of Therapy).

Betaxolol tablets, USP should not be given to patients with untreated pheochromocytoma.

PRECAUTIONS:

General:

Beta-adrenoceptor blockade can cause reduction of intraocular pressure. Since betaxolol hydrochloride is marketed as an ophthalmic solution for treatment of glaucoma, patients should be told that betaxolol tablets, USP may interfere with the glaucoma-screening test. Withdrawal may lead to a return of increased intraocular pressure. Patients receiving beta-adrenergic blocking agent orally and beta-blocking ophthalmic solutions should be observed for potential additive effects either on the intraocular pressure or on the known systemic effects of beta-blockade.

The value of using beta-blockers in psoriatic patients should be carefully weighed since they have been reported to cause an aggravation in psoriasis.

Impaired Hepatic or Renal Function:

Betaxolol tablets, USP is primarily metabolized in the liver to metabolites that are inactive and then excreted by the kidneys; clearance is somewhat reduced in patients with renal failure but little changed in patients with hepatic disease. Dosage reductions have not routinely been necessary when hepatic insufficiency is present (see Dosage and Administration) but patients should be observed. Patients with severe renal impairment and those on dialysis require a reduced dose. (See Dosage and Administration).

Information For Patients:

Patients, especially those with evidence of coronary artery insufficiency, should be warned against interruption or discontinuation of betaxolol tablets, USP therapy without the physician’s advice.

Although cardiac failure rarely occurs in appropriately selected patients, patients being treated with beta-adrenergic blocking agents should be advised to consult a physician at the first sign or symptom of failure.

Patients should know how they react to this medicine before they operate automobiles and machinery or engage in other tasks requiring alertness. Patients should contact their physician if any difficulty in breathing occurs, and before surgery of any type. Patients should inform their physicians, ophthalmologist, or dentists that they are taking betaxolol tablets, USP. Patients with diabetes should be warned that beta-blockers may mask tachycardia occurring with hypoglycemia.

Drug Interactions:

The following drugs have been coadministered with betaxolol tablets, USP and have not altered its pharmacokinetics: cimetidine, nifedipine, chlorthalidone, and hydrochlorothiazide. Concomitant administration of betaxolol tablets, USP with the oral anticoagulant warfarin has been shown not to potentiate the anticoagulant effect of warfarin.

Catecholamine-depleting drugs (e.g., reserpine) may have an additive effect when given with beta-blocking agents. Patients treated with a beta-adrenergic receptor blocking agent plus a catecholamine depletor should therefore be closely observed for evidence of hypotension or marked bradycardia, which may produce vertigo, syncope, or postural hypotension.

Should it be decided to discontinue therapy in patients receiving beta-blockers and clonidine concurrently, the beta-blocker should be discontinued slowly over several days before the gradual withdrawal of clonidine.

Literature reports suggest that oral calcium antagonists may be used in combination with beta-adrenergic blocking agents when heart function is normal, but should be avoided in patients with impaired cardiac function. Hypotension, AV conduction disturbances, and left ventricular failure have been reported in some patients receiving beta-adrenergic blocking agents when an oral calcium antagonist was added to the treatment regimen. Hypotension was more likely to occur if the calcium antagonist were a dihydropyridine derivative, e.g., nifedipine, while left ventricular failure and AV conduction disturbances, including complete heart block, were more likely to occur with either verapamil or diltiazem.

Both digitalis glycosides and beta-blockers slow atrioventricular conduction and decrease heart rate. Concomitant use can increase the risk of bradycardia.

Amiodarone is an antiarrhythmic agent with negative chronotropic properties that may be additive to those seen with beta blockers.

Disopyramide is a Type I antiarrhythmic drug with potent negative inotropic and chronotropic effects. Disopyramide has been associated with severe bradycardia, asystole and heart failure when administered with beta blockers.

Particular care should be taken when using anesthetic agents which depress the myocardium, such as ether, cyclopropane, and trichloroethylene (see Warnings, Major Surgery).

Risk of anaphylactic reaction:

Although it is known that patients on beta-blockers may be refractory to epinephrine in the treatment of anaphylactic shock, beta-blockers can, in addition, interfere with the modulation of allergic reaction and lead to an increased severity and/or frequency of attacks. Severe allergic reactions including anaphylaxis have been reported in patients exposed to a variety of allergens either by repeated challenge, or accidental contact, and with diagnostic or therapeutic agents while receiving beta-blockers. Such patients may be unresponsive to the usual doses of epinephrine used to treat allergic reaction.

Carcinogenesis, Mutagenesis, Impairment of Fertility:

Lifetime studies with betaxolol HCl in mice at oral dosages of 6, 20, and 60 mg/kg/day (up to 90 x the maximum recommended human dose [MRHD] based on 60 kg body weight) and in rats at 3, 12, or 48 mg/kg/day (up to 72 x MRHD) showed no evidence of a carcinogenic effect. In a variety of in vitro and in vivo bacterial and mammalian cell assays, betaxolol HCl was nonmutagenic. Betaxolol did not adversely effect fertility or mating performance of male or female rats at doses up to 256 mg/kg/day (380 x MRHD).

Pregnancy:

Pregnancy Category C. In a study in which pregnant rats received betaxolol at doses of 4, 40, or 400 mg/kg/day, the highest dose (600 x MRHD) was associated with increased postimplantation loss, reduced litter size and weight, and an increased incidence of skeletal and visceral abnormalities, which may have been a consequence of drug-related maternal toxicity. Other than a possible increased incidence of incomplete descent of testes and sternebral reductions, betaxolol at 4 mg/kg/day and 40 mg/kg/day (6 x MRHD and 60 x MRHD) caused no fetal abnormalities. In a second study with a different strain of rat, 200 mg betaxolol/kg/day (300 x MRHD) was associated with maternal toxicity and an increase in resorptions, but no tetratogenicity. In a study in which pregnant rabbits received doses of 1, 4, 12, or 36 mg betaxolol/kg/day (54 x MRHD), a marked increase in postimplantation loss occurred at the highest dose, but no drug-related teratogenicity was observed. The rabbit is more sensitive to betaxolol than other species because of higher bioavailability resulting from saturation of the first-pass effect. In a peri- and postnatal study in rats at doses of 4, 32, and 256 mg betaxolol/kg/day (380 x MRHD), the highest dose was associated with a marked increase in total litter loss within 4 days postpartum. In surviving offspring, growth and development were also affected.

There are no adequate and well-controlled studies in pregnant women. Betaxolol tablets, USP should be used during pregnancy only if the potential benefit justifies the potential risk to the fetus. Beta-blockers reduce placental perfusion, which may result in intrauterine fetal death, immature and premature deliveries. In addition, adverse effects (especially hypoglycemia and bradycardia) may occur in fetus.

Neonatal period

The beta-blocker action persists in the neonate for several days after birth to a treated mother: there is an increased risk of cardiac and pulmonary complications in the neonate in the postnatal period. Bradycardia, respiratory distress and hypoglycemia have also been reported. Accordingly, attentive surveillance of the neonate (heart rate and blood glucose for the first 3 to 5 days of life) in a specialized setting is recommended.

Nursing Mothers:

Since betaxolol is excreted in human milk in sufficient amounts to have pharmacological effects in the infant, caution should be exercised when betaxolol tablets, USP is administered to a nursing mother.

Pediatric Use:

Safety and effectiveness in pediatric patients have not been established.

Elderly Patients:

Betaxolol tablets, USP may produce bradycardia more frequently in elderly patients. In general, patients 65 years of age and older had a higher incidence rate of bradycardia (heart rate <50 BPM) than younger patients in U.S. clinical trials. In a double-blind study in Europe, 19 elderly patients (mean age = 82) received betaxolol tablets, USP 20 mg daily. Dosage reduction to 10 mg or discontinuation was required for 6 patients due to bradycardia (See Dosage and Administration).

ADVERSE REACTIONS:

Most adverse reactions have been mild and transient and are typical of beta-adrenergic blocking agents, e.g., bradycardia, fatigue, dyspnea, and lethargy. Withdrawal of therapy in U.S. and European controlled clinical trials has been necessary in about 3.5% of patients, principally because of bradycardia, fatigue, dizziness, headache, and impotence. Frequency estimates of adverse events were derived from controlled studies in which adverse reactions were volunteered and elicited in U.S. studies and volunteered and/or elicited in European studies.

In the U.S., the placebo-controlled hypertension studies lasted for 4 weeks, while the active-controlled hypertension studies has a 22- to 24- week double-blind phase. The following doses were studied: Betaxolol tablets, USP-5, 10, 20, and 40 mg once daily; atenolol-25, 50, and 100 mg once daily; and propranolol-40, 80, and 160 mg b.i.d.

Betaxolol tablets, USP, like other beta-blockers, has been associated with the development of antinuclear antibodies (ANA) (e.g. lupus erythematosus). In controlled clinical studies, conversion of ANA from negative to positive occurred in 5.3% of the patients treated with betaxolol tablets, USP, 6.3% of the patients treated with atenolol, 4.9% of the patients treated with propranolol, and 3.2% of the patients treated with placebo.

Betaxolol adverse events reported with a 2% or greater frequency, and selected events with lower frequency, in U.S. controlled studies are:

Of the above adverse reactions associated with the use of betaxolol, only bradycardia was clearly dose related, but there was a suggestion of dose relatedness for fatigue, lethargy, and dyspepsia.

In Europe, the placebo-controlled study lasted for 4 weeks, while the comparative studies had a 4- to 52-week double-blind phase. The following doses were studied: Betaxolol 20 and 40 mg once daily and atenolol 100 mg once daily.

From European controlled hypertension clinical trials, the following adverse events reported by 2% or more patients and selected events with lower frequency are presented:

The only adverse event whose frequency clearly rose with increasing dose was bradycardia. Elderly patients were especially susceptible to bradycardia, which in some cases responded to dose-reduction (see Precautions).

The following selected (potentially important) adverse events have been reported at an incidence of less than 2% in U.S. controlled hypertension and open, long-term clinical studies, European controlled clinical trials, or in marketing experience. It is not known whether a causal relationship exists between betaxolol tablets, USP and these events; they are listed to alert the physician to a possible relationship:

Autonomic: flushing, salivation, sweating.

Body as a whole: allergy, fever, malaise, pain, rigors.

Cardiovascular: angina pectoris, arrhythmia, atrioventricular block, heart failure, hypertension, hypotension, myocardial infarction, thrombosis, syncope.

Central and peripheral nervous system: ataxia, neuralgia, neuropathy, numbness, speech disorder, stupor, tremor, twitching.

Gastrointestinal: anorexia, constipation, dry mouth, increased appetite, mouth ulceration, rectal disorders, vomiting, dysphagia.

Hearing and Vestibular: earache, labyrinth disorders, tinnitus, deafness.

Hematologic: anemia, leucocytosis, lymphadenopathy, purpura, thrombocytopenia.

Liver and biliary: increased AST, increased ALT.

Metabolic and nutritional: acidosis, diabetes, hypercholesterolemia, hyperglycemia, hyperkalemia, hyperlipemia, hyperuricemia, hypokalemia, weight gain, weight loss, thirst, increased LDH.

Musculoskeletal: arthropathy, neck pain, muscle cramps, tendonitis.

Psychiatric: abnormal thinking, amnesia, impaired concentration, confusion, emotional lability, hallucinations, decreased libido.

Reproductive disorders: Female: breast pain, breast fibroadenosis, menstrual disorder; Male: Peyronie’s disease, prostatitis.

Respiratory: bronchitis, bronchospasm, cough, epistaxis, flu, pneumonia, sinusitis.

Skin: alopecia, eczema, erythematous rash, hypertrichosis, pruritus, skin disorders.

Special senses: abnormal taste, taste loss.

Urinary system: cystitis, dysuria, micturition disorder, oliguria, proteinuria, abnormal renal function, renal pain.

Vascular: cerebrovascular disorder, intermittent claudication, leg cramps, peripheral ischemia, thrombophlebitis.

Vision: abnormal lacrimation, abnormal vision, blepharitis, ocular hemorrhage, conjunctivitis, dry eyes, iritis, cataract, scotoma.

Potential Adverse Effects: Although not reported in clinical studies with betaxolol tablets, USP, a variety of adverse effects have been reported with other beta-adrenergic blocking agents and may be considered potential adverse effects of betaxolol tablets, USP:

Central nervous system: Reversible mental depression progressing to catatonia, an acute reversible syndrome characterized by disorientation for time and place, short-term memory loss, emotional lability with slightly clouded sensorium, and decreased performance on neuropsychometric tests.

Allergic: Fever combined with aching and sore throat, laryngospasm, respiratory distress.

Hematologic: Agranulocytosis, thrombocytopenic purpura, and nonthrombocytopenic purpura.

Gastrointestinal: Mesenteric arterial thrombosis, ischemic colitis.

Miscellaneous: Raynaud’s phenomena. There have been reports of skin rashes and/or dry eyes associated with the use of beta-adrenergic blocking drugs. The reported incidence is small, and in most cases, the symptoms have cleared when treatment was withdrawn. Discontinuation of the drug should be considered if any such reaction is not otherwise explicable. Patients should be closely monitored following cessation of therapy.

The oculomucocutaneous syndrome associated with the beta-blocker practolol has not been reported with betaxolol tablets, USP during investigational use and extensive foreign experience. However, dry eyes have been reported.

OVERDOSAGE:

No specific information on emergency treatment of overdosage with betaxolol tablets, USP is available. The most common effects expected are bradycardia, congestive heart failure, hypotension, bronchospasm, and hypoglycemia. In one acute overdosage of betaxolol, a 16-year-old female recovered fully after ingesting 460 mg.

Oral LD50s are 350 to 400 mg betaxolol/kg in mice and 860 to 980 mg/kg in rats.

In the case of overdosage, treatment with betaxolol tablets, USP should be stopped and the patient carefully observed. Hemodialysis or peritoneal dialysis does not remove substantial amounts of the drug. In addition to gastric lavage, the following therapeutic measures are suggested if warranted:

Hypotension: Use sympathomimetic pressor drug therapy, such as dopamine, dobutamine, or norepinephrine. In refractory cases of overdosage of other beta-blockers, the use of glucagon hydrochloride has been reported to be useful.

Bradycardia: Atropine should be administered. If there is no response to vagal blockade, isoproterenol should be administered cautiously (see Warnings: Major surgery). In refractory cases the use of a transvenous cardiac pacemaker may be considered.

Acute cardiac failure: Conventional therapy including digitalis, diuretics, and oxygen should be instituted immediately.

Bronchospasm: Use a ß2- agonist. Additional therapy with aminophylline may be considered.

Heart block (2nd- or 3rd-degree): Use isoproterenol or a transvenous cardiac pacemaker.

DOSAGE AND ADMINISTRATION:

The initial dose of betaxolol tablets, USP in hypertension is ordinarily 10 mg once daily either alone or added to diuretic therapy. The full antihypertensive effect is usually seen within 7 to 14 days. If the desired response is not achieved the dose can be doubled after 7 to 14 days. Increasing the dose beyond 20 mg has not been shown to produce a statistically significant additional antihypertensive effect; but the 40-mg dose has been studied and is well tolerated. An increased effect (reduction) on heart rate should be anticipated with increasing dosage. If monotherapy with betaxolol tablets, USP does not produce the desired response, the addition of a diuretic agent or other antihypertensive should be considered (see PRECAUTIONS, Drug Interactions).

Dosage Adjustments For Specific Patients:

Patients with renal failure:

In patients with renal impairment, clearance of betaxolol declines with decreasing renal function.

In patients with severe renal impairment and those undergoing dialysis, the initial dose of betaxolol tablets, USP is 5 mg once daily. If the desired response is not achieved, dosage may be increased by 5 mg/day increments every 2 weeks to a maximum dose of 20 mg/day.

Patients with hepatic disease:

Patients with hepatic disease do not have significantly altered clearance. Dosage adjustments are not routinely needed.

Elderly patients:

Consideration should be given to reduction in the starting dose to 5 mg in elderly patients. These patients are especially prone to beta-blocker-induced bradycardia, which appears to be dose related and sometimes responds to reductions in dose.

Cessation of therapy:

If withdrawal of betaxolol tablets, USP therapy is planned, it should be achieved gradually over a period of about 2 weeks. Patients should be carefully observed and advised to limit physical activity to a minimum.

HOW SUPPLIED:

Betaxolol Tablets, USP are available as follows:

Betaxolol Tablets, USP 10 mg: (Each tablet contains 10 mg betaxolol HCl equivalent to 8.94 mg betaxolol) are as white, round, film-coated biconvex tablets, debossed "k" above bisect "13" on one side and plain on the other.

Bottles of 100, NDC 10702-013-01

Betaxolol Tablets, USP 20 mg: (Each tablet contains 20 mg betaxolol HCl equivalent to 17.88 mg betaxolol) are as white, round, film-coated biconvex tablets, debossed "K" above "14" on one side and plain on the other.

Bottles of 100, NDC 10702-014-01

Store at 20° to 25°C (68° to 77°F) with excursions permitted between 15° to 30°C (59° to 86°F) [See USP Controlled Room Temperature].

Dispense in a tight container as defined in the USP, with a child-resistant closure (as required).

Manufactured by:

KVK-TECH, INC.

110 Terry Drive

Newtown, PA 18940

ID # 006037/09 04/2020

Manufacturer’s Code: 10702

Packging Labeling:

10 mg Label:

NDC 10702-013-01

Betaxolol

Tablets, USP

10 mg

100 TABLETS

Rx Only

KVK-TECH, INC.

20 mg Label:

NDC 10702-014-01

Betaxolol

Tablets, USP

20 mg

100 TABLETS

Rx Only

KVK-TECH, INC.